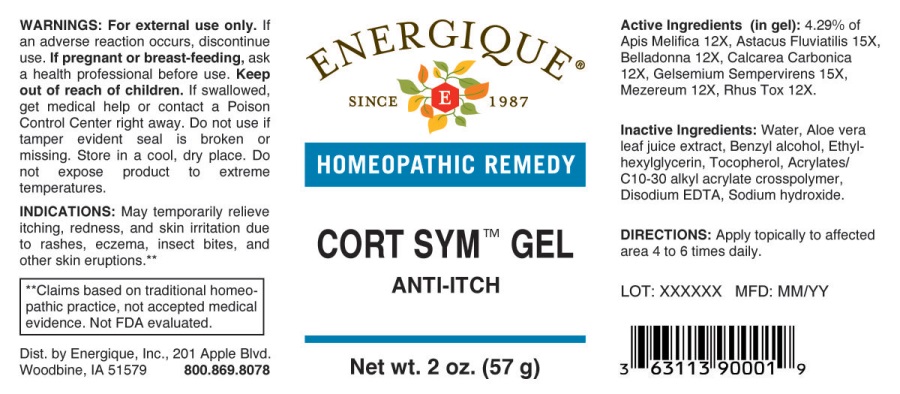 DRUG LABEL: Cort Sym
NDC: 44911-0142 | Form: GEL
Manufacturer: Energique, Inc.
Category: homeopathic | Type: HUMAN OTC DRUG LABEL
Date: 20241024

ACTIVE INGREDIENTS: APIS MELLIFERA 12 [hp_X]/1 g; ATROPA BELLADONNA 12 [hp_X]/1 g; OYSTER SHELL CALCIUM CARBONATE, CRUDE 12 [hp_X]/1 g; DAPHNE MEZEREUM BARK 12 [hp_X]/1 g; TOXICODENDRON PUBESCENS LEAF 12 [hp_X]/1 g; ASTACUS ASTACUS 15 [hp_X]/1 g; GELSEMIUM SEMPERVIRENS ROOT 15 [hp_X]/1 g
INACTIVE INGREDIENTS: WATER; CARBOMER INTERPOLYMER TYPE A (ALLYL SUCROSE CROSSLINKED); BENZYL ALCOHOL; ETHYLHEXYLGLYCERIN; TOCOPHEROL; SODIUM HYDROXIDE; ALOE VERA LEAF; EDETATE DISODIUM

DRUG FACTS:

ACTIVE INGREDIENTS:

(in gel): 4.29% of Apis Mellifica 12X, Astacus Fluviatilis 15X, Belladonna 12X, Calcarea Carbonica 12X, Gelsemium Sempervirens 15X,

Mezereum 12X, Rhus Tox 12X.

INDICATIONS:

May temporarily relieve itching, redness, and skin irritation due to rashes, eczema, insect bites, and other skin eruptions**

**Claims based on traditional homeopathic practice, not accepted medical evidence. Not FDA evaluated.

WARNINGS:

For external use only. If an adverse reaction occurs, discontinue use.

If pregnant or breast-feeding, ask a health professional before use.

Keep out of reach of children. If swallowed, get medical help or contact a Poison Control Center right away.

Do not use if tamper evident seal is broken or missing.

Store in a cool, dry place. Do not expose product to extreme temperatures.

Keep out of reach of children. If swallowed, get medical help or contact a Poison Control Center right away.

DIRECTIONS:

Apply topically to affected area 4 to 6 times daily.

INDICATIONS:

May temporarily relieve itching, redness, and skin irritation due to rashes, eczema, insect bites, and other skin eruptions**

**Claims based on traditional homeopathic practice, not accepted medical evidence. Not FDA evaluated.

INACTIVE INGREDIENTS:

Water, Aloe Barbadensis Leaf Juice, Benzyl Alcohol, Ethylhexylglycerin, Tocopherol, Acrylates/C10-30 Alkyl Acrylate Crosspolymer, Disodium EDTA, Sodium Hydroxide.

QUESTIONS:

Dist. by Energique, Inc., 201 Apple Blvd.

Woodbine, IA 51579 800.869.8078

PACKAGE LABEL DISPLAY:

ENERGIQUE
SINCE 1987
HOMEOPATHIC REMEDY
CORT SYM GEL
ANTI-ITCH
Net wt. 2 oz. (57 g)